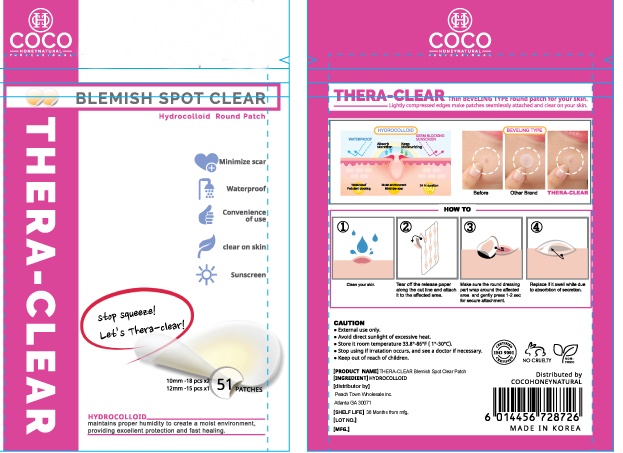 DRUG LABEL: THERA-CLEAR
NDC: 80938-301 | Form: PATCH
Manufacturer: Peach Town Wholesale Inc.
Category: otc | Type: HUMAN OTC DRUG LABEL
Date: 20201019

ACTIVE INGREDIENTS: CARBOXYMETHYLCELLULOSE 60 g/100 g
INACTIVE INGREDIENTS: PECTIN

Active Ingredient

Hydrocolloid

Uses

Thin Beveling Type round patch for your skin.

Lightly compressed edges make partches seamlessly attached and clear on your skin.

Warning

External use only.

Avoid direct sunlight of excessive heat.

Stop use Ask a doctor

Stopp using if irratation occurs, and see a doctor if necessary.

Keep out of reach of children

Directions

1. Clean your skin.

2. Tear off the release paper along the cut line and attach it to the affected area.

3. Make sure the round dressing part wrap around the affected area and gently press 1-2 sec for secure attachment.

4. Replace if it swell white due to absorbtion of secretion.

other information

Store it room temperature 33.8º-86ºF(1º-30ºC).

Inactive ingredient

Pectin

Purpose

Acne

label

80938-301-01